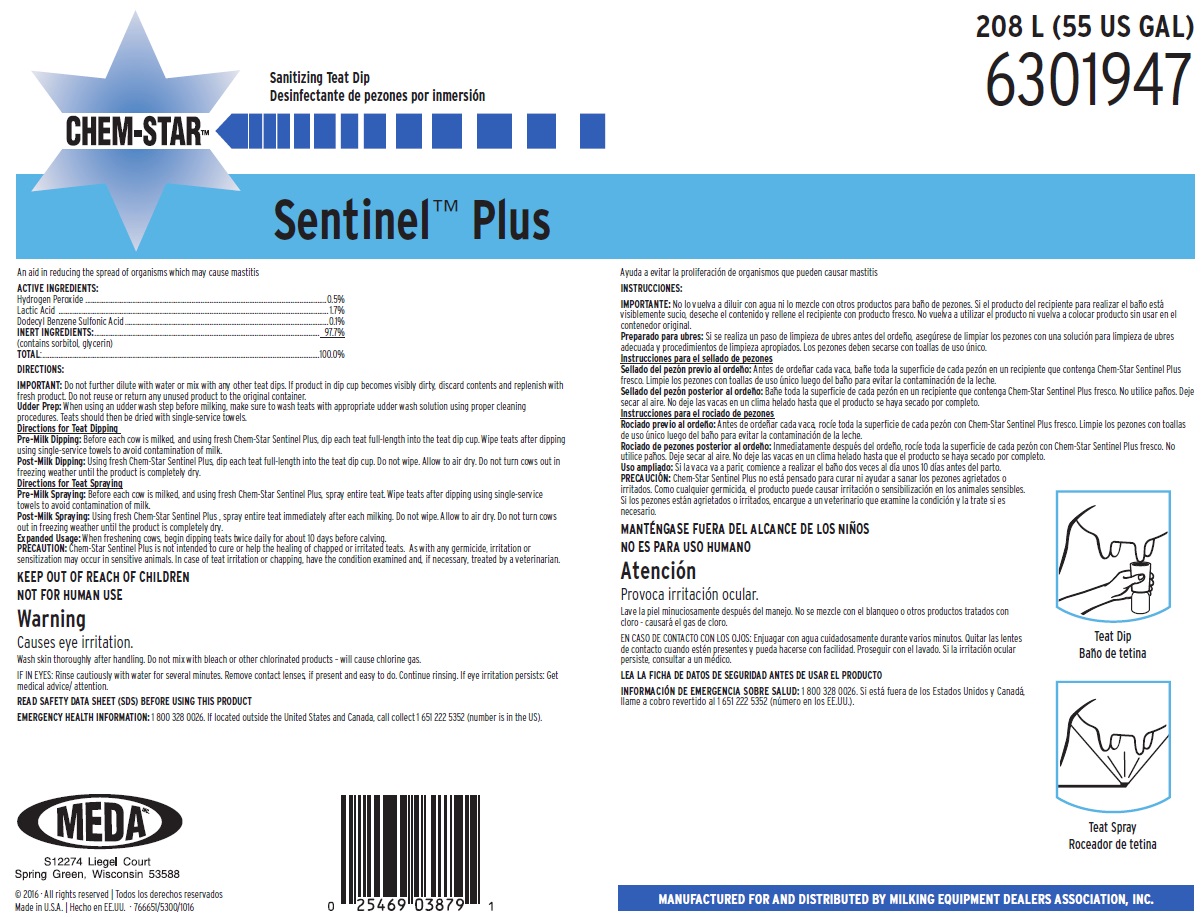 DRUG LABEL: Chem-Star Sentinel Plus
NDC: 59511-412 | Form: SOLUTION
Manufacturer: MEDA Inc.
Category: animal | Type: OTC ANIMAL DRUG LABEL
Date: 20170110

ACTIVE INGREDIENTS: HYDROGEN PEROXIDE 5 mg/1 mL; DODECYLBENZENESULFONIC ACID 5 mg/1 mL; LACTIC ACID 17 mg/1 mL
INACTIVE INGREDIENTS: WATER; GLYCERIN; SORBITOL

KEEP OUT OF REACH OF CHILDREN

NOT FOR HUMAN USE

WARNING

Causes eye irritation

Wash skin thoroughly after handling. Do not mix with bleach or other chlorinated products – will cause chlorine gas.

DIRECTIONS:

IMPORTANT: Do not further dilute with water or mix with any other teat dips. If product in dip cup becomes visibly dirty, discard contents and replenish with fresh product. Do not reuse or return any unused product to the original container.

Udder Prep: When using an udder wash step before milking, make sure to wash teats with appropriate udder wash solution using proper cleaning procedures. Teats should then be dried with single-service towels.

Directions for Teat Dipping

Pre-Milk Dipping: Before each cow is milked, and using fresh Chem-Star Sentinel Plus, dip each teat full-length into the teat dip cup. Wipe teats after dipping using single-service towels to avoid contamination of milk.

Post-Milk Dipping: Using fresh Chem-Star Sentinel Plus, dip each teat full-length into the teat dip cup. Do not wipe. Allow to air dry. Do not turn cows out in freezing weather until the product is completely dry.

Directions for Teat Spraying

Pre-Milk Spraying: Before each cow is milked, and using fresh Chem-Star Sentinel Plus, spray entire teat. Wipe teats after dipping using single-service towels to avoid contamination of milk.

Post-Milk Spraying: Using fresh Chem-Star Sentinel Plus , spray entire teat immediately after each milking. Do not wipe. Allow to air dry. Do not turn cows out in freezing weather until the product is completely dry.

Expanded Usage: When freshening cows, begin dipping teats twice daily for about 10 days before calving.

PRECAUTION: Chem-Star Sentinel Plus is not intended to cure or help the healing of chapped or irritated teats. As with any germicide, irritation or sensitization may occur in sensitive animals. In case of teat irritation or chapping, have the condition examined and, if necessary, treated by a veterinarian.

OTHER SAFETY INFORMATION

IF IN EYES: Rinse cautiously with water for several minutes. Remove contact lenses, if present and easy to do. Continue rinsing. If eye irritation persists: Get medical advice/ attention.

READ SAFETY DATA SHEET (SDS) BEFORE USING THIS PRODUCT

EMERGENCY HEALTH INFORMATION: 1 800 328 0026. If located outside the United States and Canada, call collect 1 651 222 5352 (number is in the US).

PRINCIPAL DISPLAY PANEL/REPRESENTATIVE LABEL

208 L (55 US GAL)

6301947

Sanitizing Teat Dip

CHEM-STAR™

An aid in reducing the spread of organisms which may cause mastitis

ACTIVE INGREDIENTS:

Hydrogen Peroxide............................................ 0.5%

Lactic Acid....................................................... 1.7%

Dodecyl Benzene Sulfonic Acid............................ 0.5%

INERT INGREDIENTS:..................................... 97.3%

(contains sorbitol, glycerin)

TOTAL:........................................................... 100.0%

MEDA
S12274 Liegel Court
Spring Green, Wisconsin 53588

©2016 - All rights reserved

Made in U.S.A. - 766651/5300/1016

MANUFACTURED FOR AND DISTRIBUTED BY MILKING EQUIPMENT DEALERS ASSOCIATION, INC.